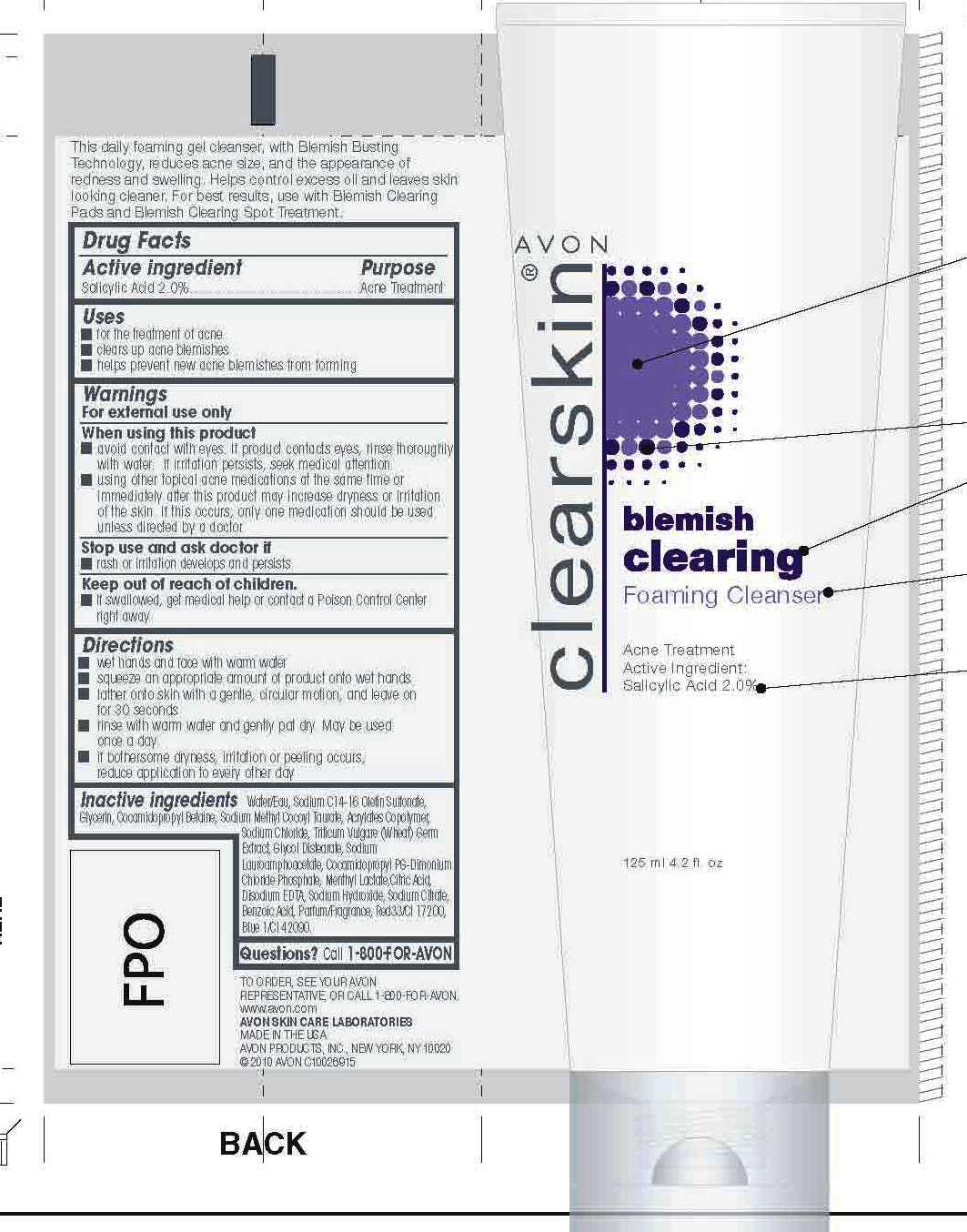 DRUG LABEL: Clearskin
NDC: 10096-0200 | Form: GEL
Manufacturer: New Avon LLC
Category: otc | Type: HUMAN OTC DRUG LABEL
Date: 20190101

ACTIVE INGREDIENTS: SALICYLIC ACID 20 mg/1 mL
INACTIVE INGREDIENTS: WATER

Clearskin Blemish Clearing Foaming Cleanser

Active ingredient

Salicylic Acid 2.0%................

Purpose

.........Acne Treatment

Uses

- for the treatment of acne
- clears up acne blemishes
- helps prevent new acne blemishes from forming

Warnings
For external use only

When using this product

- avoid contact with eyes. If product contacts eyes, rinse thoroughly with water. If irritation persists, seek medical attention
- using other topical acne products at the same time or immediately after this product may increase dryness or irritation of the skin. If this occurs, only one medication should be used unless directed by a doctor

Stop use and ask a doctor if

- rash or irritation develops and persists

Keep out of reach of children. If swallowed, get medical
help or contact a Poison Control Center right away.

Directions

- wet hands and face with warm water
- squeeze an appropriate amount of product onto wet hands
- lather onto skin with a gentle, circular motion, and leave on for 30 seconds
- rinse with warm water and gently pat dry. May be used once a day.
- if bothersome dryness, irritation or peeling occurs, reduce application to every other day

Inactive ingredients

WATER/EAU
SODIUM C14-16 OLEFIN SULFONATE
GLYCERIN
COCAMIDOPROPYL BETAINE
SODIUM METHYL COCOYL TAURATE
ACRYLATES COPOLYMER
SODIUM CHLORIDE
TRITICUM VULGARE (WHEAT) GERM EXTRACT
GLYCOL DISTEARATE
SODIUM LAUROAMPHOACETATE
COCAMIDOPROPYL PG-DIMONIUM CHLORIDE PHOSPHATE
MENTHYL LACTATE
CITRIC ACID
DISODIUM EDTA
SODIUM HYDROXIDE
SODIUM CITRATE
BENZOIC ACID
PARFUM/FRAGRANCE
RED 33/CI 17200
BLUE 1/CI 42090

Questions? Call 1-800-FOR-AVON